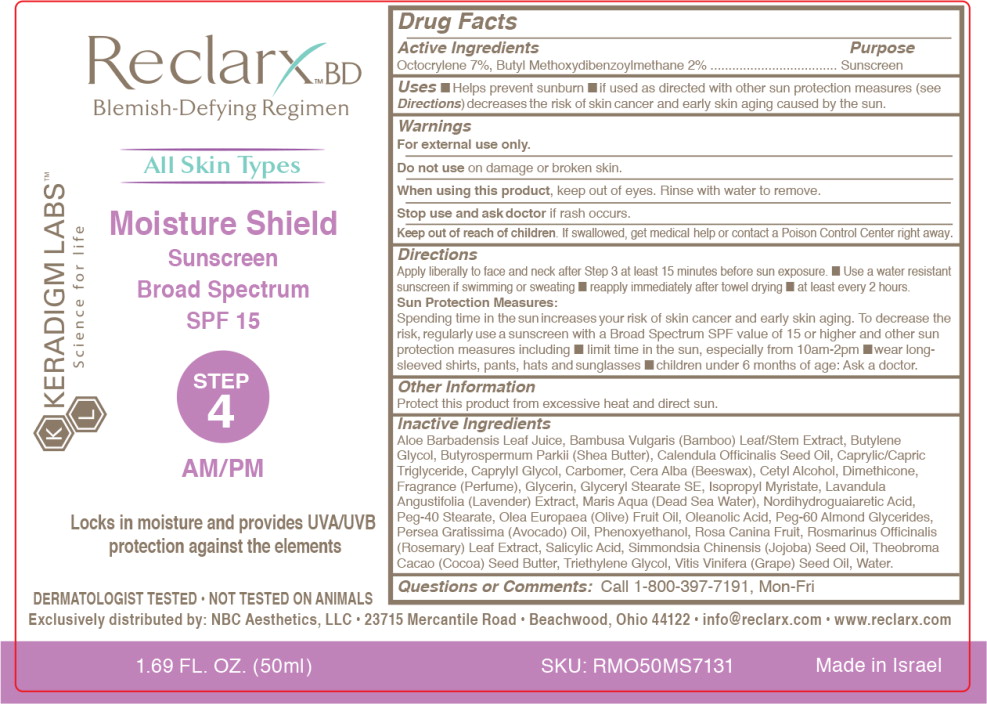 DRUG LABEL: Reclarx Moisture Shield
NDC: 61402-7131 | Form: CREAM
Manufacturer: NBC Aesthetics, LLC
Category: otc | Type: HUMAN OTC DRUG LABEL
Date: 20150527

ACTIVE INGREDIENTS: OCTOCRYLENE 7 g/100 mL; AVOBENZONE 2 g/100 mL
INACTIVE INGREDIENTS: WATER; MEDIUM-CHAIN TRIGLYCERIDES; GLYCERYL STEARATE SE; CETYL ALCOHOL; ISOPROPYL MYRISTATE; GLYCERIN; CALENDULA OFFICINALIS SEED OIL; ALOE VERA LEAF; SHEA BUTTER; PHENOXYETHANOL; GRAPE SEED OIL; SALICYLIC ACID; BUTYLENE GLYCOL; PEG-60 ALMOND GLYCERIDES; CAPRYLYL GLYCOL; CARBOMER HOMOPOLYMER TYPE C; MASOPROCOL; OLEANOLIC ACID; WHITE WAX; PEG-40 STEARATE; COCOA BUTTER; LAVANDULA ANGUSTIFOLIA FLOWERING TOP; JOJOBA OIL; DIMETHICONE; BAMBUSA VULGARIS TOP; OLIVE OIL; ROSA CANINA FRUIT OIL; ROSEMARY; AVOCADO OIL; TRIETHYLENE GLYCOL

Drug Facts

Active Ingredients

Octocrylene 7%, Butyl Methoxydibenzoylmethane 2%

Purpose

Sunscreen

Uses

- Helps prevent sunburn
- if used as directed with other sun protection measures (see Directions) decreases the risk of skin cancer and early skin aging caused by the sun.

Warnings

For external use only.

Do not use on damage or broken skin.

When using this product, keep out of eyes. Rinse with water to remove.

Stop use and ask doctor if rash occurs.

Keep out of reach of children. If swallowed, get medical help or contact a Poison Control Center right away.

Directions

Apply liberally to face and neck after Step 3 at least 15 minutes before sun exposure.

- Use a water resistant sunscreen if swimming or sweating
- reapply immediately after towel drying
- at least every 2 hours.

Sun Protection Measures:

Spending time in the sun increases your risk of skin cancer and early skin aging. To decrease the risk, regularly use a sunscreen with a Broad Spectrum SPF value of 15 or higher and other sun protection measures including

- limit time in the sun, especially from 10am-2pm
- wear long-sleeved shirts, pants, hats and sunglasses
- children under 6 months of age: Ask a doctor.

Other Information

Protect this product from excessive heat and direct sun.

Inactive Ingredients

Aloe Barbadensis Leaf Juice, Bambusa Vulgaris (Bamboo) Leaf/Stem Extract, Butylene Glycol, Butyrospermum Parkii (Shea Butter), Calendula Officinalis Seed Oil, Caprylic/Capric Triglyceride, Caprylyl Glycol, Carbomer, Cera Alba (Beeswax), Cetyl Alcohol, Dimethicone, Fragrance (Perfume), Glycerin, Glyceryl Stearate SE, Isopropyl Myristate, Lavandula Angustifolia (Lavender) Extract, Maris Aqua (Dead Sea Water), Nordihydroguaiaretic Acid, Peg-40 Stearate, Olea Europaea (Olive) Fruit Oil, Oleanolic Acid, Peg-60 Almond Glycerides, Persea Gratissima (Avocado) Oil, Phenoxyethanol, Rosa Canina Fruit, Rosmarinus Officinalis (Rosemary) Leaf Extract, Salicylic Acid, Simmondsia Chinensis (Jojoba) Seed Oil, Theobroma Cacao (Cocoa) Seed Butter, Triethylene Glycol, Vitis Vinifera (Grape) Seed Oil, Water.

Questions or Comments:

Call 1-800-397-7191, Mon-Fri

Principal Display Panel - Bottle Label

Reclarx™ BD

Blemish-Defying Regimen

All Skin Types

Moisture Shield

Sunscreen

Broad Spectrum

SPF 15

STEP
4

AM/PM

Locks In moisture and provides UVA/UVB
protection against the elements

DERMATOLOGIST TESTED • NOT TESTED ON ANIMALS

Exclusively distributed by: NBC Aesthetics, LLC • 23715 Mercantile Road • Beachwood, Ohio 44122 • info@reclarx.com • www.reclarx.com